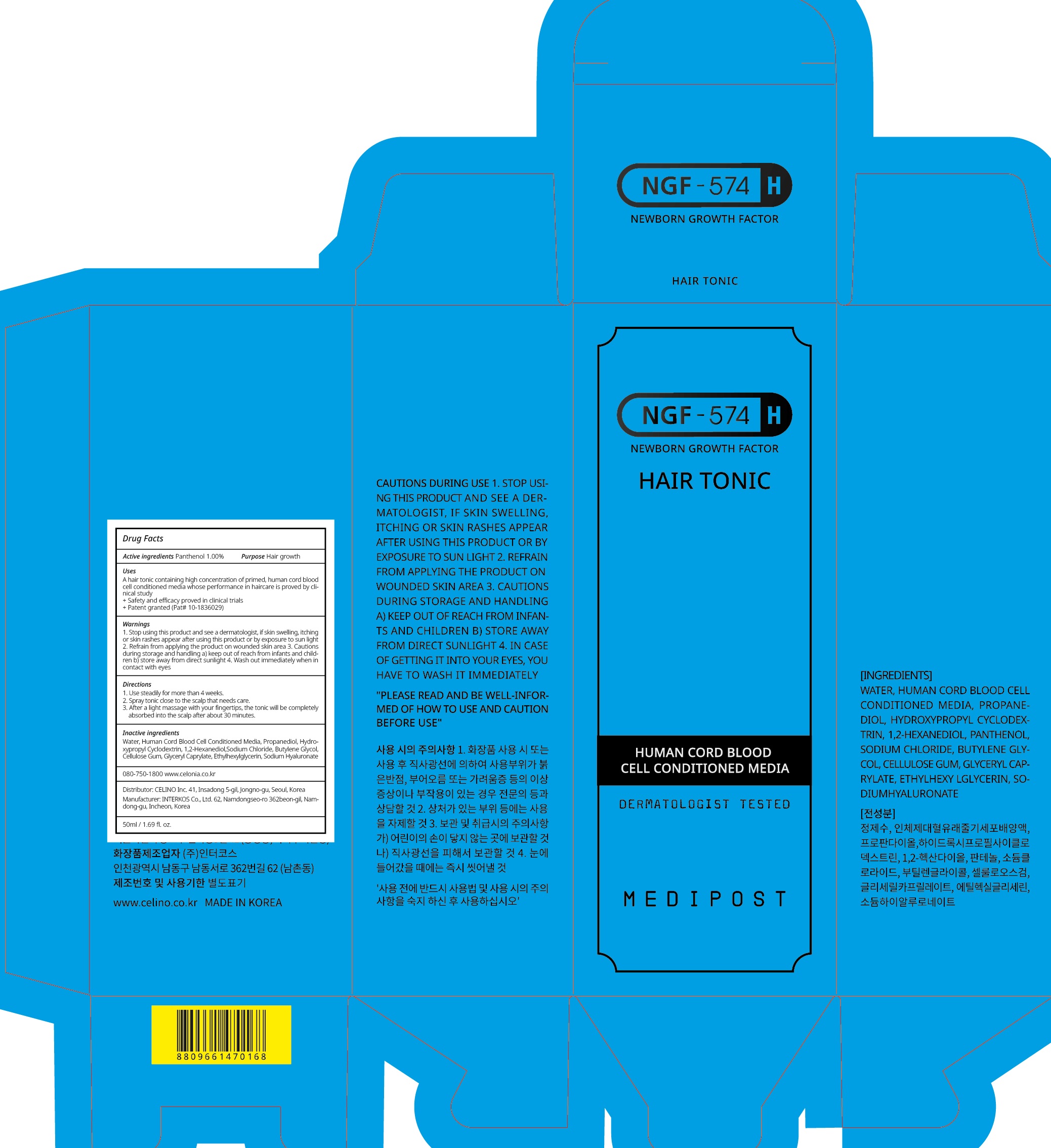 DRUG LABEL: NGF 574H HAIR TONIC
NDC: 73655-070 | Form: LIQUID
Manufacturer: Celino Inc.
Category: otc | Type: HUMAN OTC DRUG LABEL
Date: 20200310

ACTIVE INGREDIENTS: Panthenol 0.50 g/50 mL
INACTIVE INGREDIENTS: Water; 1,2-Hexanediol

ACTIVE INGREDIENT

Active ingredients: Panthenol 1.00%

INACTIVE INGREDIENT

Inactive ingredients:

Water, Human Cord Blood Cell Conditioned Media, Propanediol, Hydroxypropyl Cyclodextrin, 1,2-Hexanediol,Sodium Chloride, Butylene Glycol, Cellulose Gum, Glyceryl Caprylate, Ethylhexylglycerin, Sodium Hyaluronate

PURPOSE

Purpose: Hair growth

WARNINGS

1. Stop using this product and see a dermatologist, if skin swelling, itching or skin rashes appear after using this product or by exposure to sun light

2. Refrain from applying the product on wounded skin area

3. Cautions during storage and handling a) keep out of reach from infants and children b) store away from direct sunlight

4. Wash out immediately when in contact with eyes

KEEP OUT OF REACH OF CHILDREN

keep out of reach from infants and children

QUESTIONS

080-750-1800

www.celonia.co.kr

Uses

A hair tonic containing high concentration of primed, human cord blood cell conditioned media whose performance in haircare is proved by clinical study
+ Safety and efficacy proved in clinical trials
+ Patent granted (Pat# 10-1836029)

Directions

1. Use steadily for more than 4 weeks.
2. Spray tonic close to the scalp that needs care.
3. After a light massage with your fingertips, the tonic will be completely absorbed into the scalp after about 30 minutes.